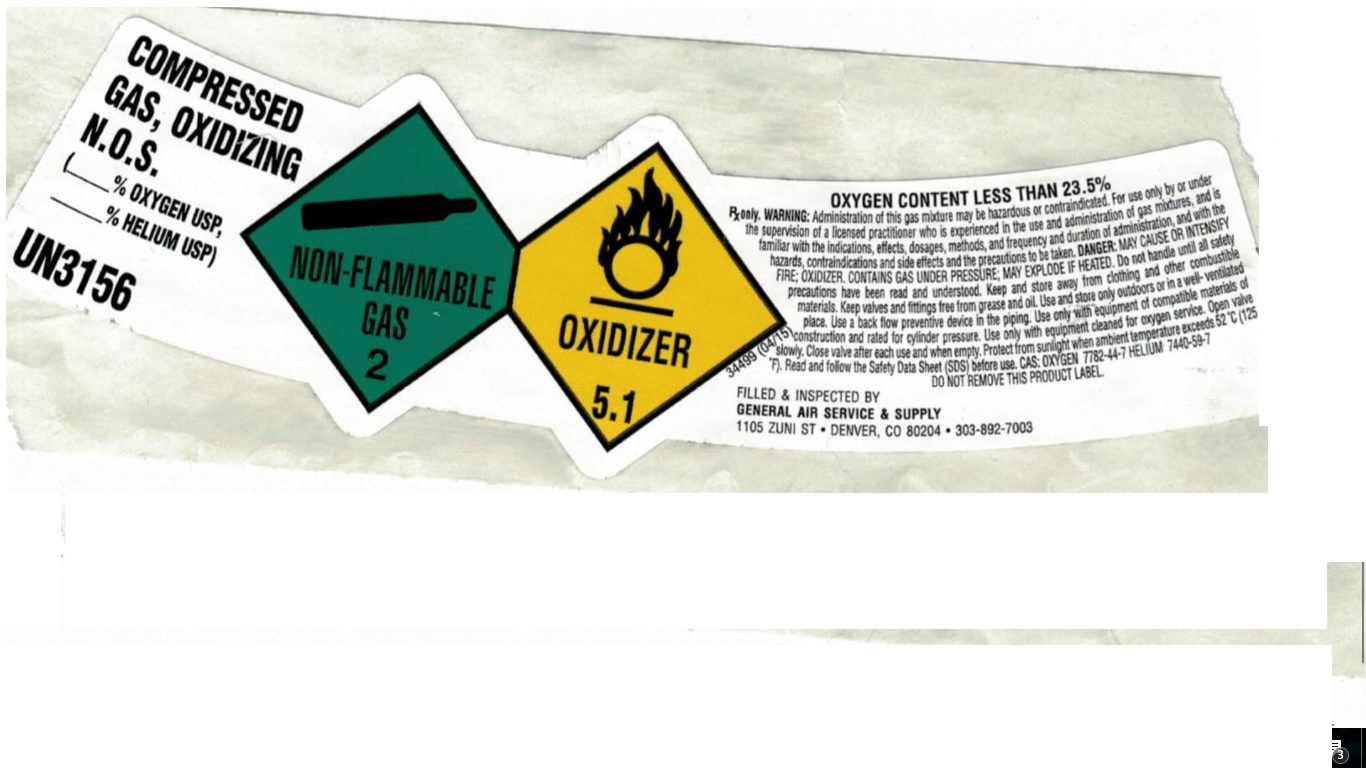 DRUG LABEL: Helium/Oxygen Mixture 70/30
NDC: 21220-158 | Form: GAS
Manufacturer: General Air Service & Supply Co
Category: prescription | Type: HUMAN PRESCRIPTION DRUG LABEL
Date: 20251126

ACTIVE INGREDIENTS: OXYGEN 300 mL/1 L
INACTIVE INGREDIENTS: HELIUM 700 mL/1 L

Helium/Oxygen Mixture 70/30

PACKAGE LABEL

COMRESSED GAS, OXIDIZING N.O.S
UN3156
OXYGEN CONTENT LESS THAN 23.5%
Rx only. WARNING: Administration of this gas mixture may be hazardous or contraindicated. For use only by or under the supervision of a licensed practitioner who is experienced in the use and administration of gas mixtures, and is familiar with the indications, effects, dosages, methods, and frequency and duration of administration, and with the hazards, contraindications and side effects and the precautions to be taken. DANGER: MAY CAUSE OR INTENSIFY FIRE; OXIDIZER. CONTAINS GAS UNDER PRESSURE; MAY EXPLODE IF HEATED. Do not handle until all safety precautions have been read and understood. Keep and store away from clothing and other combustible materials. Keep valves and fittings free from grease and oil. Use and store only outdoors or in a well-ventilated place. Use a back flow preventive device in the piping. Use only with equipment of compatible materials of construction and rated for cylinder pressure. Use only with equipment cleaned for oxygen service. Open valve slowly. Close valve after each use and when empty. Protect from sunlight when ambient temperature exceeds 52 C (125 F). Read and follow the Safety Data Sheet (SDS) before use. CAS: OXYGEN 7782-44-7 HELIUM 7440-59-7
DO NOT REMOVE THIS PRODUCT LABEL.
FILLED & INSPECTED BY
GENERAL AIR SERVICE & SUPPLY
1105 ZUNI ST
DENVER, CO 80204
303-892-7003